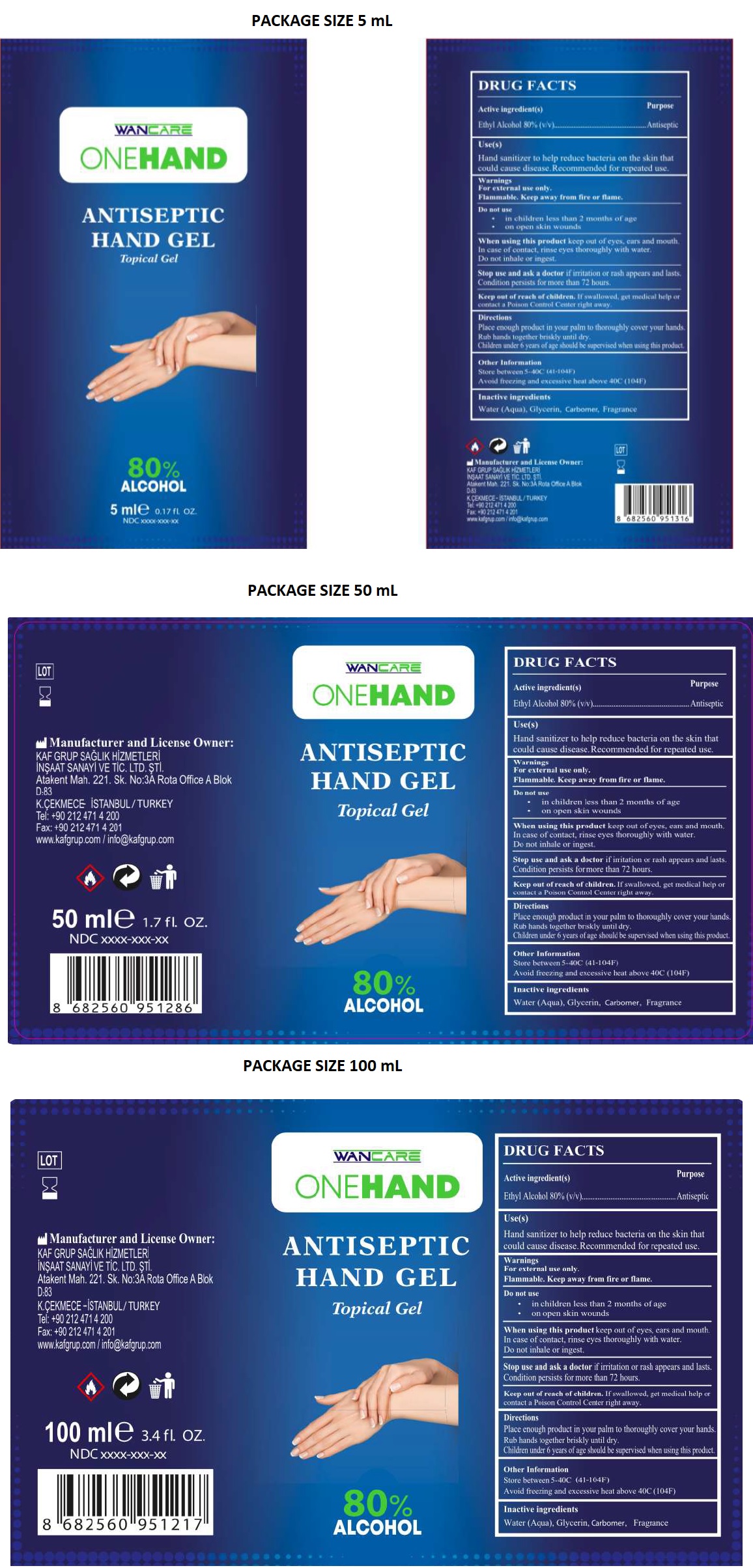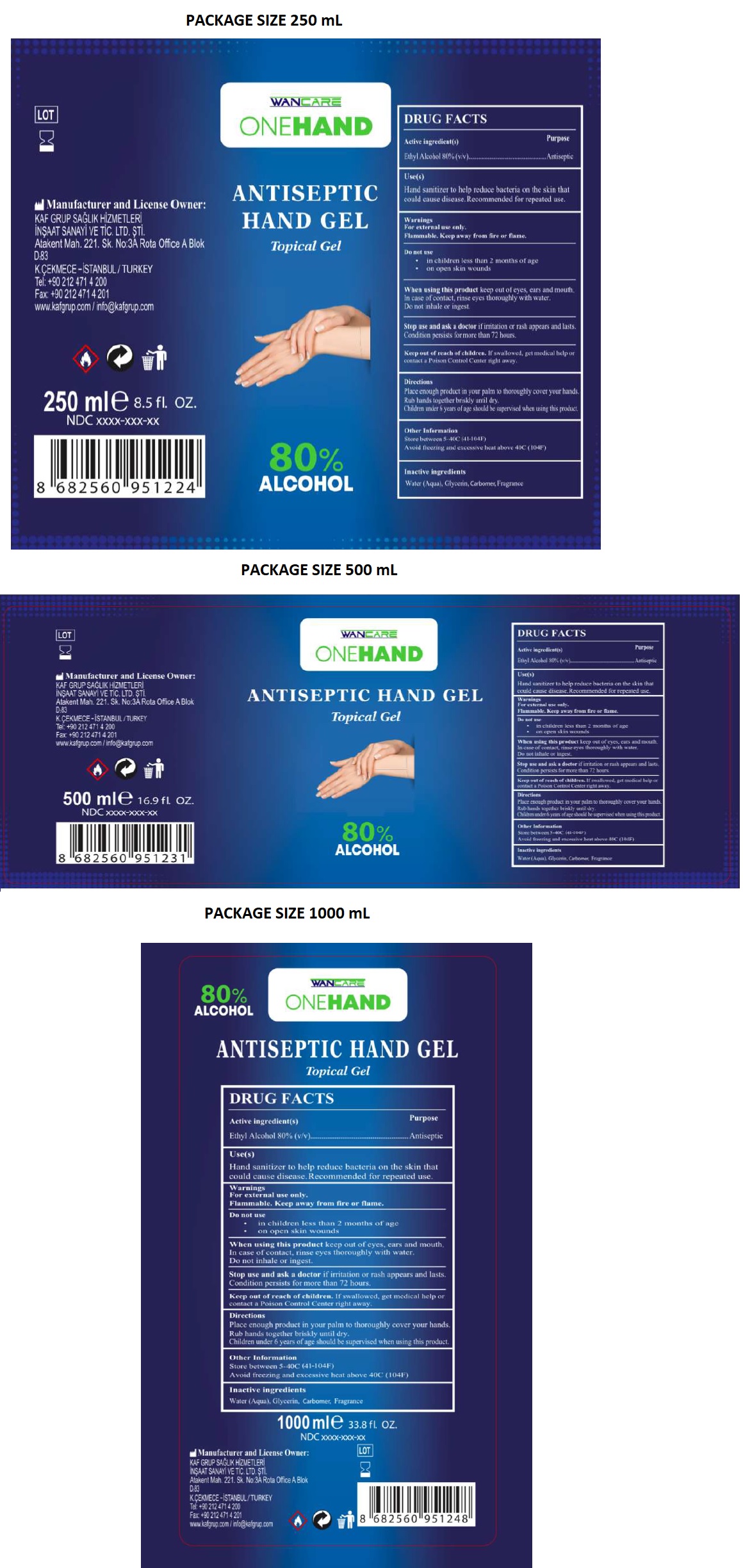 DRUG LABEL: WANCARE
NDC: 81314-202 | Form: GEL
Manufacturer: KAF GRUP SAGLIK HIZMETLERI INSAAT SANAYI VE TICARET LIMITED SIRKETI
Category: otc | Type: HUMAN OTC DRUG LABEL
Date: 20201231

ACTIVE INGREDIENTS: ALCOHOL 80 mL/100 mL
INACTIVE INGREDIENTS: WATER; GLYCERIN; CARBOMER HOMOPOLYMER, UNSPECIFIED TYPE

WANCARE ONEHAND ANTISEPTIC HAND GEL

Active ingredient(s)

Ethyl Alcohol 80% (v/v)

Purpose

Antiseptic

Use(s)

Hand sanitizer to help reduce bacteria on the skin that could cause disease. Recommended for repeated use.

Warnings

For external use only.

Flammable. Keep away from fire or flame.

Do not use

• in children less than 2 months of age
• on open skin wounds

When using this product keep out of eyes, ears and mouth. In case of contact, rinse eyes thoroughly with water. Do not inhale or ingest.

Stop use and ask a doctor if irritation or rash appears and lasts. Condition persists for more than 72 hours.

Keep out of reach of children. If swallowed, get medical help or contact a Poison Control Center right away.

Directions

Place enough product in your palm to thoroughly cover your hands.

Rub hands together briskly until dry.

Children under 6 years of age should be supervised when using this product.

Other Information

Store between 5-40C (41-104F)

Avoid freezing and excessive heat above 40C (104F)

Inactive ingredients

Water (Aqua), Glycerin, Carbomer, Fragrance

80% ALCOHOL

Topical Gel

Manufacturer and License Owner:

KAF GRUP SAGLIK HIZMETLERI

INSAAT SANAYI VE TIC. LTD. STI.

Atakent Mah. 221. Sk. No:3A Rota Office A Blok

D:83

K.CEKMECE -ISTANBUL/TURKEY

Tel: +90 212 471 4 200

Fax: +90 212 471 4 201

www.kafgrup.com / info@kafgrup.com